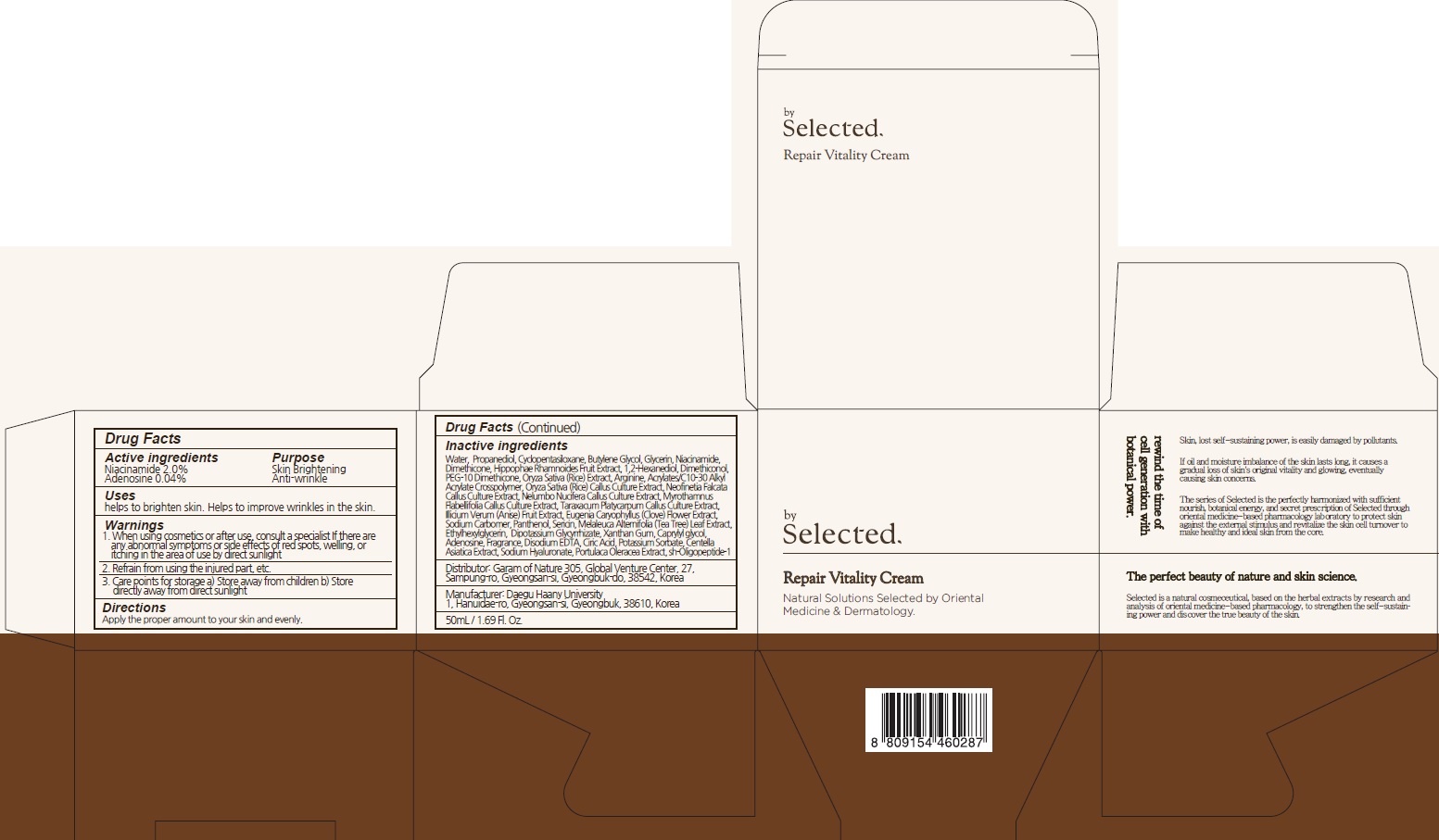 DRUG LABEL: by Selected Repair Vitality
NDC: 73509-040 | Form: CREAM
Manufacturer: Garam Of Nature
Category: otc | Type: HUMAN OTC DRUG LABEL
Date: 20210803

ACTIVE INGREDIENTS: Niacinamide 1.00 g/50 mL; ADENOSINE 0.02 g/50 mL
INACTIVE INGREDIENTS: Water; Propanediol

ACTIVE INGREDIENTS

NIACINAMIDE 2.0%
ADENOSINE 0.04%

INACTIVE INGREDIENT

Water, Propanediol, Cyclopentasiloxane, Butylene Glycol, Glycerin, Dimethicone, Hippophae Rhamnoides Fruit Extract, 1,2-Hexanediol, Dimethiconol, PEG-10 Dimethicone, Oryza Sativa (Rice) Extract, Arginine, Acrylates/C10-30 Alkyl Acrylate Crosspolymer, Oryza Sativa (Rice) Callus Culture Extract, Neofinetia Falcata Callus Culture Extract, Nelumbo Nucifera Callus Culture Extract, Myrothamnus Flabellifolia Callus Culture Extract, Taraxacum Platycarpum Callus Culture Extract, Illicium Verum (Anise) Fruit Extract, Eugenia Caryophyllus (Clove) Flower Extract,
Sodium Carbomer, Panthenol, Sericin, Melaleuca Alternifolia (Tea Tree) Leaf Extract, Ethylhexylglycerin, Dipotassium Glycyrrhizate, Xanthan Gum, Caprylyl glycol, Fragrance, Disodium EDTA, Ciric Acid, Potassium Sorbate, Centella Asiatica Extract, Sodium Hyaluronate, Portulaca Oleracea Extract, sh-Oligopeptide-1

PURPOSE

Skin Brightening
Anti-wrinkle

WARNINGS

1. When using cosmetics or after use, consult a specialist If there are any abnormal symptoms or side effects of red spots, welling, or itching in the area of use by direct sunlight.
2. Refrain from using the injured part, etc.
3. Care points for storage a) Store away from children b) Store directly away from direct sunlight

KEEP OUT OF REACH OF CHILDREN

Store away from children

Uses

Helps to brighten skin.
Helps to improve wrinkles in the skin.

Directions

Apply the proper amount to your skin and evenly.